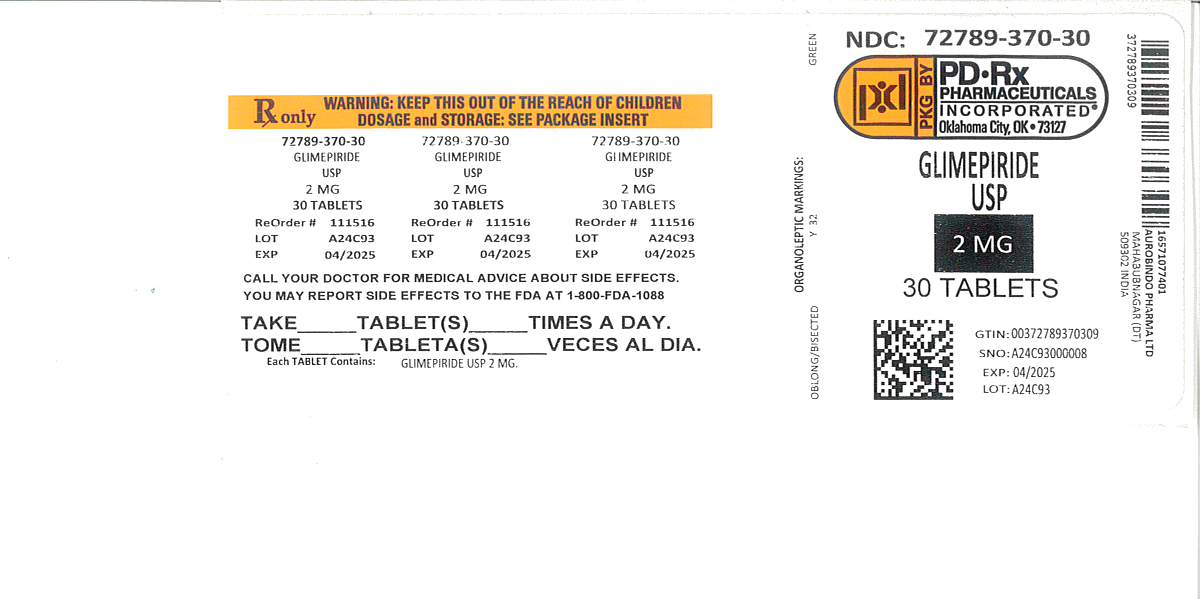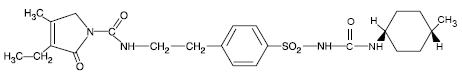 DRUG LABEL: Glimepiride
NDC: 72789-370 | Form: TABLET
Manufacturer: PD-Rx Pharmaceuticals, Inc.
Category: prescription | Type: HUMAN PRESCRIPTION DRUG LABEL
Date: 20260226

ACTIVE INGREDIENTS: GLIMEPIRIDE 2 mg/1 1
INACTIVE INGREDIENTS: LACTOSE MONOHYDRATE; MAGNESIUM STEARATE; MICROCRYSTALLINE CELLULOSE; POVIDONE K25; SODIUM STARCH GLYCOLATE TYPE A POTATO; FERRIC OXIDE YELLOW; FD&C BLUE NO. 2

HIGHLIGHTS OF PRESCRIBING INFORMATION

These highlights do not include all the information needed to use GLIMEPIRIDE TABLETS safely and effectively. See full prescribing information for GLIMEPIRIDE TABLETS.
GLIMEPIRIDE tablets, for oral use
Initial U.S. Approval: 1995

1 INDICATIONS AND USAGE

Glimepiride is a sulfonylurea indicated as an adjunct to diet and exercise to improve glycemic control in adults with type 2 diabetes mellitus (1).
Limitations of Use:

- Not for treating type 1 diabetes mellitus or diabetic ketoacidosis (1).

2 DOSAGE AND ADMINISTRATION

- Recommended starting dose is 1 mg or 2 mg once daily. Increase in 1 mg or 2 mg increments no more frequently than every 1 to 2 weeks based on glycemic response. Maximum recommended dose is 8 mg once daily. (2.1)
- Administer with breakfast or first meal of the day. (2.1)
- Use 1 mg starting dose and titrate slowly in patients at increased risk for hypoglycemia (e.g., elderly, patients with renal impairment). (2.1)

3 DOSAGE FORMS AND STRENGTHS

Tablets (scored): 1 mg, 2 mg, and 4 mg (3)

4 CONTRAINDICATIONS

- Hypersensitivity to glimepiride or any of the product’s ingredients (4)
- Hypersensitivity to sulfonamide derivatives (4)

5 WARNINGS AND PRECAUTIONS

- Hypoglycemia: May be severe. Ensure proper patient selection, dosing, and instructions, particularly in at-risk populations (e.g., elderly, renally impaired) and when used with other anti-diabetic medications. (5.1)
- Hypersensitivity Reactions: Postmarketing reports include anaphylaxis, angioedema and Stevens-Johnson syndrome. If a reaction is suspected, promptly discontinue glimepiride, assess for other potential causes for the reaction, and institute alternative treatment for diabetes. (5.2)
- Hemolytic Anemia: Can occur if glucose 6-phosphate dehydrogenase (G6PD) deficient. Consider a non-sulfonylurea alternative. (5.3)
- Potential Increased Risk of Cardiovascular Mortality with Sulfonylureas: Inform patient of risks, benefits and treatment alternatives. (5.4)
- Macrovascular Outcomes: No clinical studies establishing conclusive evidence of macrovascular risk reduction with glimepiride or any other anti-diabetic drug. (5.5)

6 ADVERSE REACTIONS

Common adverse reactions in clinical trials (≥5% and more common than with placebo) include hypoglycemia, headache, nausea, and dizziness (6.1).
To report SUSPECTED ADVERSE REACTIONS, contact Rising Pharma Holdings, Inc. at 1(844) 874-7464 or FDA at 1-800-FDA-1088 orwww.fda.gov/medwatch.

7 DRUG INTERACTIONS

- Certain medications may affect glucose metabolism, requiring glimepiride dose adjustment and close monitoring of blood glucose. (7.1)
- Miconazole: Severe hypoglycemia can occur when glimepiride and oral miconazole are used concomitantly. (7.2)
- Cytochrome P450 2C9 interactions: Inhibitors and inducers of cytochrome P450 2C9 may affect glycemic control by altering glimepiride plasma concentrations. (7.3)
- Colesevelam: Coadministration may reduce glimepiride absorption. Glimepiride should be administered at least 4 hours prior to colesevelam. (2.1,7.4)

8 USE IN SPECIFIC POPULATIONS

- Pediatric Patients: Not recommended because of adverse effects on body weight and hypoglycemia. (8.4)
- Geriatric or Renally Impaired Patients: At risk for hypoglycemia with glimepiride. Use caution in dose selection and titration, and monitor closely. (8.5, 8.6)

FULL PRESCRIBING INFORMATION

1 INDICATIONS AND USAGE

Glimepiride tablets are indicated as an adjunct to diet and exercise to improve glycemic control in adults with type 2 diabetes mellitus [see Clinical Studies (14.1)].
Limitations of Use
Glimepiride tablets should not be used for the treatment of type 1 diabetes mellitus or diabetic ketoacidosis, as it would not be effective in these settings.

2 DOSAGE AND ADMINISTRATION

2.1 Recommended Dosing

Glimepiride tablets should be administered with breakfast or the first main meal of the day.
The recommended starting dose of glimepiride tablets is 1 mg or 2 mg once daily. Patients at increased risk for hypoglycemia (e.g., the elderly or patients with renal impairment) should be started on 1 mg once daily [see Warnings and Precautions (5.1)and Use in Specific Populations (8.5, 8.6)].
After reaching a daily dose of 2 mg, further dose increases can be made in increments of 1 mg or 2 mg based upon the patient’s glycemic response. Uptitration should not occur more frequently than every 1 to 2 weeks. A conservative titration scheme is recommended for patients at increased risk for hypoglycemia [see Warnings and Precautions (5.1)and Use in Specific Populations (8.5, 8.6)] .
The maximum recommended dose is 8 mg once daily.
Patients being transferred to glimepiride tablets from longer half-life sulfonylureas (e.g., chlorpropamide) may have overlapping drug effect for 1 to 2 weeks and should be appropriately monitored for hypoglycemia.
When colesevelam is coadministered with glimepiride, maximum plasma concentration and total exposure to glimepiride is reduced. Therefore, glimepiride tablets should be administered at least 4 hours prior to colesevelam.

3 DOSAGE FORMS AND STRENGTHS

Glimepiride is formulated as tablets of:

- 1 mg (pink colored, flat-faced, oblong uncoated tablets with notched sides at double bisect, debossed with “X” and “76” on either side of the bisect on one face and plain on the other face)
- 2 mg (light green to green colored, flat-faced, oblong uncoated tablets with notched sides at double bisect, debossed with “Y” and “32” on either side of the bisect on one face and plain on the other face)
- 4 mg (light blue to blue colored, flat-faced, oblong uncoated tablets with notched sides at double bisect, debossed with “Y” and “34” on either side of the bisect on one face and plain on the other face)

4 CONTRAINDICATIONS

Glimepiride tablets are contraindicated in patients with a history of a hypersensitivity reaction to:

- Glimepiride or any of the product’s ingredients [see Warnings and Precautions (5.2)].
- Sulfonamide derivatives: Patients who have developed an allergic reaction to sulfonamide derivatives may develop an allergic reaction to glimepiride tablets. Do not use glimepiride tablets in patients who have a history of an allergic reaction to sulfonamide derivatives.

5 WARNINGS AND PRECAUTIONS

5.1 Hypoglycemia

All sulfonylureas, including glimepiride, can cause severe hypoglycemia [see Adverse Reactions (6.1)] . The patient’s ability to concentrate and react may be impaired as a result of hypoglycemia. These impairments may present a risk in situations where these abilities are especially important, such as driving or operating other machinery. Severe hypoglycemia can lead to unconsciousness or convulsions and may result in temporary or permanent impairment of brain function or death.
Patients must be educated to recognize and manage hypoglycemia. Use caution when initiating and increasing glimepiride doses in patients who may be predisposed to hypoglycemia (e.g., the elderly, patients with renal impairment, patients on other anti-diabetic medications). Debilitated or malnourished patients, and those with adrenal, pituitary, or hepatic impairment are particularly susceptible to the hypoglycemic action of glucose-lowering medications. Hypoglycemia is also more likely to occur when caloric intake is deficient, after severe or prolonged exercise, or when alcohol is ingested.
Early warning symptoms of hypoglycemia may be different or less pronounced in patients with autonomic neuropathy, the elderly, and in patients who are taking beta-adrenergic blocking medications or other sympatholytic agents. These situations may result in severe hypoglycemia before the patient is aware of the hypoglycemia.

5.2 Hypersensitivity Reactions

There have been postmarketing reports of hypersensitivity reactions in patients treated with glimepiride, including serious reactions such as anaphylaxis, angioedema, and Stevens-Johnson syndrome [see Adverse Reactions (6.2)] . If a hypersensitivity reaction is suspected, promptly discontinue glimepiride, assess for other potential causes for the reaction, and institute alternative treatment for diabetes.

5.3 Hemolytic Anemia

Sulfonylureas can cause hemolytic anemia in patients with glucose 6-phosphate dehydrogenase (G6PD) deficiency. Because glimepiride is a sulfonylurea, use caution in patients with G6PD deficiency and consider the use of a non-sulfonylurea alternative. There are also postmarketing reports of hemolytic anemia in patients receiving glimepiride who did not have known G6PD deficiency [see Adverse Reactions (6.2)] .

5.4 Increased Risk of Cardiovascular Mortality with Sulfonylureas

The administration of oral hypoglycemic drugs has been reported to be associated with increased cardiovascular mortality as compared to treatment with diet alone or diet plus insulin. This warning is based on the study conducted by the University Group Diabetes Program (UGDP), a long-term, prospective clinical trial designed to evaluate the effectiveness of glucose-lowering drugs in preventing or delaying vascular complications in patients with non-insulin-dependent diabetes. The study involved 823 patients who were randomly assigned to one of four treatment groups.
UGDP reported that patients treated for 5 to 8 years with diet plus a fixed dose of tolbutamide (1.5 grams per day) had a rate of cardiovascular mortality approximately 2 and a half times that of patients treated with diet alone. A significant increase in total mortality was not observed, but the use of tolbutamide was discontinued based on the increase in cardiovascular mortality, thus limiting the opportunity for the study to show an increase in overall mortality. Despite controversy regarding the interpretation of these results, the findings of the UGDP study provide an adequate basis for this warning. The patient should be informed of the potential risks and advantages of glimepiride and of alternative modes of therapy.
Although only one drug in the sulfonylurea class (tolbutamide) was included in this study, it is prudent from a safety standpoint to consider that this warning may also apply to other oral hypoglycemic drugs in this class, in view of their close similarities in mode of action and chemical structure.

5.5 Macrovascular Outcomes

There have been no clinical studies establishing conclusive evidence of macrovascular risk reduction with glimepiride or any other anti-diabetic drug.

6 ADVERSE REACTIONS

The following serious adverse reactions are discussed in more detail below and elsewhere in the labeling:

- Hypoglycemia [see Warnings and Precautions (5.1)]
- Hemolytic anemia [see Warnings and Precautions (5.3)]

6.1 Clinical Trials Experience

Because clinical trials are conducted under widely varying conditions, adverse reaction rates observed in the clinical trials of a drug cannot be directly compared to rates in the clinical trials of another drug and may not reflect the rates observed in practice.

Approximately 2,800 patients with type 2 diabetes have been treated with glimepiride in the controlled clinical trials. In these trials, approximately 1,700 patients were treated with glimepiride for at least 1 year. In clinical trials, the most common adverse reactions with glimepiride were hypoglycemia, dizziness, asthenia, headache, and nausea.

Table 1 summarizes adverse events, other than hypoglycemia, that were reported in 11 pooled placebo-controlled trials, whether or not considered to be possibly or probably related to study medication. Treatment duration ranged from 13 weeks to 12 months. Terms that are reported represent those that occurred at an incidence of ≥5% among glimepiride-treated patients and more commonly than in patients who received placebo.

Table 1: Eleven Pooled Placebo-Controlled Trials ranging from 13 weeks to 12 months: Adverse Events (excluding hypoglycemia) Occurring in ≥5% of Glimepiride-treated Patients and at a Greater Incidence than with Placebo*

 | Glimepiride N=745 % | Placebo N=294 %
Headache | 8.2 | 7.8
Accidental Injury† | 5.8 | 3.4
Flu Syndrome | 5.4 | 4.4
Nausea | 5 | 3.4
Dizziness | 5 | 2.4

*Glimepiride doses ranged from 1 to 16 mg administered daily

†Insufficient information to determine whether any of the accidental injury events were associated with hypoglycemia

Hypoglycemia

In a randomized, double-blind, placebo-controlled monotherapy trial of 14 weeks duration, patients already on sulfonylurea therapy underwent a 3-week washout period then were randomized to glimepiride 1 mg, 4 mg, 8 mg, or placebo. Patients randomized to glimepiride 4 mg or 8 mg underwent forced-titration from an initial dose of 1 mg to these final doses, as tolerated [see Clinical Studies (14.1)]. The overall incidence of possible hypoglycemia (defined by the presence of at least one symptom that the investigator believed might be related to hypoglycemia; a concurrent glucose measurement was not required) was 4% for glimepiride 1 mg, 17% for glimepiride 4 mg, 16% for glimepiride 8 mg and 0% for placebo. All of these events were self-treated.

In a randomized, double-blind, placebo-controlled monotherapy trial of 22 weeks duration, patients received a starting dose of either 1 mg glimepiride or placebo daily. The dose of glimepiride was titrated to a target fasting plasma glucose of 90 to 150 mg/dL. Final daily doses of glimepiride were 1, 2, 3, 4, 6, or 8 mg [see Clinical Studies (14.1)] . The overall incidence of possible hypoglycemia (as defined above for the 14-week trial) for glimepiride vs. placebo was 19.7% vs. 3.2%. All of these events were self-treated.

Weight gain
Glimepiride, like all sulfonylureas, can cause weight gain [see Clinical Studies (14.1)] .

Allergic Reactions
In clinical trials, allergic reactions, such as pruritus, erythema, urticaria, and morbilliform or maculopapular eruptions, occurred in less than 1% of glimepiride-treated patients. These may resolve despite continued treatment with glimepiride. There are postmarketing reports of more serious allergic reactions (e.g., dyspnea, hypotension, shock) [see Warnings and Precautions (5.2)] .

Laboratory Tests

Elevated serum alanine aminotransferase (ALT)
In 11 pooled placebo-controlled trials of glimepiride, 1.9% of glimepiride-treated patients and 0.8% of placebo-treated patients developed serum ALT greater than 2 times the upper limit of the reference range.

6.2 Postmarketing Experience

The following adverse reactions have been identified during postapproval use of glimepiride. Because these reactions are reported voluntarily from a population of uncertain size, it is not always possible to reliably estimate their frequency or establish a causal relationship to drug exposure.

- Serious hypersensitivity reactions, including anaphylaxis, angioedema, and Stevens-Johnson syndrome [see Warnings and Precautions (5.2)]
- Hemolytic anemia in patients with and without G6PD deficiency [see Warnings and Precautions (5.3)]
- Impairment of liver function (e.g., with cholestasis and jaundice), as well as hepatitis, which may progress to liver failure
- Porphyria cutanea tarda, photosensitivity reactions and allergic vasculitis
- Leukopenia, agranulocytosis, aplastic anemia, and pancytopenia
- Thrombocytopenia (including severe cases with platelet count less than 10,000/µL) and thrombocytopenic purpura
- Hepatic porphyria reactions and disulfiram-like reactions
- Hyponatremia and syndrome of inappropriate antidiuretic hormone secretion (SIADH), most often in patients who are on other medications or who have medical conditions known to cause hyponatremia or increase release of antidiuretic hormone
- Dysgeusia
- Alopecia

7 DRUG INTERACTIONS

7.1 Drugs Affecting Glucose Metabolism

A number of medications affect glucose metabolism and may require glimepiride dose adjustment and particularly close monitoring for hypoglycemia or worsening glycemic control.
The following are examples of medications that may increase the glucose-lowering effect of sulfonylureas including glimepiride, increasing the susceptibility to and/or intensity of hypoglycemia: oral anti-diabetic medications, pramlintide acetate, insulin, angiotensin converting enzyme (ACE) inhibitors, H2receptor antagonists, fibrates, propoxyphene, pentoxifylline, somatostatin analogs, anabolic steroids and androgens, cyclophosphamide, phenyramidol, guanethidine, fluconazole, sulfinpyrazone, tetracyclines, clarithromycin, disopyramide, quinolones, and those drugs that are highly protein-bound, such as fluoxetine, nonsteroidal anti-inflammatory drugs, salicylates, sulfonamides, chloramphenicol, coumarins, probenecid and monoamine oxidase inhibitors. When these medications are administered to a patient receiving glimepiride, monitor the patient closely for hypoglycemia. When these medications are withdrawn from a patient receiving glimepiride, monitor the patient closely for worsening glycemic control.
The following are examples of medications that may reduce the glucose-lowering effect of sulfonylureas including glimepiride, leading to worsening glycemic control: danazol, glucagon, somatropin, protease inhibitors, atypical antipsychotic medications (e.g., olanzapine and clozapine), barbiturates, diazoxide, laxatives, rifampin, thiazides and other diuretics, corticosteroids, phenothiazines, thyroid hormones, estrogens, oral contraceptives, phenytoin, nicotinic acid, sympathomimetics (e.g., epinephrine, albuterol, terbutaline), and isoniazid. When these medications are administered to a patient receiving glimepiride, monitor the patient closely for worsening glycemic control. When these medications are withdrawn from a patient receiving glimepiride, monitor the patient closely for hypoglycemia.
Beta-blockers, clonidine, and reserpine may lead to either potentiation or weakening of glimepiride’s glucose-lowering effect.
Both acute and chronic alcohol intake may potentiate or weaken the glucose-lowering action of glimepiride in an unpredictable fashion.
The signs of hypoglycemia may be reduced or absent in patients taking sympatholytic drugs such as beta-blockers, clonidine, guanethidine, and reserpine.

7.2 Miconazole

A potential interaction between oral miconazole and sulfonylureas leading to severe hypoglycemia has been reported. Whether this interaction also occurs with other dosage forms of miconazole is not known.

7.3 Cytochrome P450 2C9 Interactions

There may be an interaction between glimepiride and inhibitors (e.g., fluconazole) and inducers (e.g., rifampin) of cytochrome P450 2C9. Fluconazole may inhibit the metabolism of glimepiride, causing increased plasma concentrations of glimepiride which may lead to hypoglycemia. Rifampin may induce the metabolism of glimepiride, causing decreased plasma concentrations of glimepiride which may lead to worsening glycemic control.

7.4 Concomitant Administration of Colesevelam

Colesevelam can reduce the maximum plasma concentration and total exposure of glimepiride when the two are coadministered. However, absorption is not reduced when glimepiride is administered 4 hours prior to colesevelam. Therefore, glimepiride should be administered at least 4 hours prior to colesevelam.

8 USE IN SPECIFIC POPULATIONS

8.1 Pregnancy

Risk Summary

Available data from a small number of published studies and postmarketing experience with glimepiride use in pregnancy over decades have not identified any drug associated risks for major birth defects, miscarriage, or adverse maternal outcomes. However, sulfonylureas (including glimepiride) cross the placenta and have been associated with neonatal adverse reactions such as hypoglycemia. Therefore, glimepiride should be discontinued at least two weeks before expected delivery (see Clinical Considerations). Poorly controlled diabetes in pregnancy is also associated with risks to the mother and fetus (see Clinical Considerations). In animal studies (see Data), there were no effects on embryo-fetal development following administration of glimepiride to pregnant rats and rabbits at oral doses approximately 4000 times and 60 times the maximum human dose based on body surface area, respectively. However, fetotoxicity was observed in rats and rabbits at doses 50 times and 0.1 times the maximum human dose, respectively.

The estimated background risk of major birth defects is 6% to 10% in women with pre-gestational diabetes with a HbA1c >7% and has been reported to be as high as 20% to 25% in women with a HbA1c >10%. The estimated background risk of miscarriage for the indicated population is unknown. In the U.S. general population, the estimated background risk of major birth defects and miscarriage in clinically recognized pregnancies is 2% to 4% and 15% to 20%, respectively.

Clinical Considerations

Disease-associated maternal and/or embryo-fetal risk

Poorly controlled diabetes in pregnancy increases the maternal risk for diabetic ketoacidosis, preeclampsia, spontaneous abortions, preterm delivery, and delivery complications. Poorly controlled diabetes increases the fetal risk for major birth defects, still birth, and macrosomia-related morbidity.

Fetal/neonatal adverse reactions

Neonates of women with gestational diabetes who are treated with sulfonylureas during pregnancy may be at increased risk for neonatal intensive care admission and may develop respiratory distress, hypoglycemia, birth injury, and be large for gestational age. Prolonged severe hypoglycemia, lasting 4 to 10 days, has been reported in neonates born to mothers receiving a sulfonylurea at the time of delivery and has been reported with the use of agents with a prolonged half-life. Observe newborns for symptoms of hypoglycemia and respiratory distress and manage accordingly.

Dose adjustments during pregnancy and the postpartum period

Due to reports of prolonged severe hypoglycemia in neonates born to mothers receiving a sulfonylurea at the time of delivery, glimepiride should be discontinued at least two weeks before expected delivery (see Fetal/Neonatal Adverse Reactions).

Data

Animal data

In animal studies, there was no increase in congenital anomalies, but an increase in fetal deaths occurred in rats and rabbits at glimepiride doses 50 times (rats) and 0.1 times (rabbits) the maximum recommended human dose (based on body surface area). This fetotoxicity was observed only at doses inducing maternal hypoglycemia and is believed to be directly related to the pharmacologic (hypoglycemic) action of glimepiride, as has been similarly noted with other sulfonylureas.

8.2 Lactation

Risk Summary

Breastfed infants of lactating women using glimepiride should be monitored for symptoms of hypoglycemia (see Clinical Considerations). It is not known whether glimepiride is excreted in human milk and there are no data on the effects of glimepiride on milk production. Glimepiride is present in rat milk [see Data]. The developmental and health benefits of breastfeeding should be considered along with the mother's clinical need for glimepiride and any potential adverse effects on the breastfed child from glimepiride or from the underlying maternal condition.

Clinical Considerations

Monitoring for adverse reactions

Monitor breastfed infants for signs of hypoglycemia (e.g., jitters, cyanosis, apnea, hypothermia, excessive sleepiness, poor feeding, seizures).

Data

During prenatal and postnatal studies in rats, significant concentrations of glimepiride were present in breast milk and the serum of the pups. Offspring of rats exposed to high levels of glimepiride during pregnancy and lactation developed skeletal deformities consisting of shortening, thickening, and bending of the humerus during the postnatal period. These skeletal deformations were determined to be the result of nursing from mothers exposed to glimepiride.

8.4 Pediatric Use

The pharmacokinetics, efficacy and safety of glimepiride have been evaluated in pediatric patients with type 2 diabetes as described below. Glimepiride is not recommended in pediatric patients because of its adverse effects on body weight and hypoglycemia.
The pharmacokinetics of a 1 mg single dose of glimepiride was evaluated in 30 patients with type 2 diabetes (male=7; female=23) between ages 10 and 17 years. The mean (± SD) AUC(0-last)(339±203 ng•hr/mL), Cmax(102±48 ng/mL) and t1/2(3.1±1.7 hours) for glimepiride were comparable to historical data from adults (AUC(0-last)315±96 ng•hr/mL, Cmax103±34 ng/mL, and t1/25.3±4.1 hours).
The safety and efficacy of glimepiride in pediatric patients was evaluated in a single-blind, 24-week trial that randomized 272 patients (8 to 17 years of age) with type 2 diabetes to glimepiride (n=135) or metformin (n=137). Both treatment-naive patients (those treated with only diet and exercise for at least 2 weeks prior to randomization) and previously treated patients (those previously treated or currently treated with other oral antidiabetic medications for at least 3 months) were eligible to participate. Patients who were receiving oral antidiabetic agents at the time of study entry discontinued these medications before randomization without a washout period. Glimepiride was initiated at 1 mg, and then titrated up to 2, 4, or 8 mg (mean last dose 4 mg) through Week 12, targeting a self-monitored fasting fingerstick blood glucose <126 mg/dL. Metformin was initiated at 500 mg twice daily and titrated at Week 12 up to 1000 mg twice daily (mean last dose 1365 mg).
After 24 weeks, the overall mean treatment difference in HbA1c between glimepiride and metformin was 0.2%, favoring metformin (95% confidence interval -0.3% to +0.6%). Based on these results, the trial did not meet its primary objective of showing a similar reduction in HbA1c with glimepiride compared to metformin.

Table 2: Change from Baseline in HbA1C and Body Weight in Pediatric Patients Taking Glimepiride or Metformin
 | Metformin | Glimepiride
Treatment-Naive Patients* | N=69 | N=72
HbA1C (%)
Baseline (mean) | 8.2 | 8.3
Change from baseline (adjusted LS mean)† | -1.2 | -1
Adjusted Treatment Difference‡(95%CI) | 0.2 (-0.3; 0.6)
Previously Treated Patients* | N=57 | N=55
HbA1C (%)
Baseline (mean) | 9 | 8.7
Change from baseline (adjusted LS mean)† | -0.2 | 0.2
Adjusted Treatment Difference‡(95%CI) | 0.4 (-0.4; 1.2)
Body Weight (kg)* | N=126 | N=129
Baseline (mean) | 67.3 | 66.5
Change from baseline (adjusted LS mean)† | 0.7 | 2
Adjusted Treatment Difference‡(95% CI) | 1.3 (0.3; 2.3)
* Intent-to-treat population using last-observation-carried-forward for missing data (glimepiride, n=127; metformin, n=126)
† adjusted for baseline HbA1Cand Tanner Stage
‡ Difference is glimepiride – metformin with positive differences favoring metformin

The profile of adverse reactions in pediatric patients treated with glimepiride was similar to that observed in adults [see Adverse Reactions (6)] .
Hypoglycemic events documented by blood glucose values <36 mg/dL were observed in 4% of pediatric patients treated with glimepiride and in 1% of pediatric patients treated with metformin. One patient in each treatment group experienced a severe hypoglycemic episode (severity was determined by the investigator based on observed signs and symptoms).

8.5 Geriatric Use

In clinical trials of glimepiride, 1053 of 3491 patients (30%) were >65 years of age. No overall differences in safety or effectiveness were observed between these patients and younger patients, but greater sensitivity of some older individuals cannot be ruled out.
There were no significant differences in glimepiride pharmacokinetics between patients with type 2 diabetes ≤65 years (n=49) and those >65 years (n=42) [see Clinical Pharmacology (12.3)] .
Glimepiride is substantially excreted by the kidney. Elderly patients are more likely to have renal impairment. In addition, hypoglycemia may be difficult to recognize in the elderly [see Dosage and Administration (2.1)and Warnings and Precautions (5.1)]. Use caution when initiating glimepiride and increasing the dose of glimepiride in this patient population.

8.6 Renal Impairment

To minimize the risk of hypoglycemia, the recommended starting dose of glimepiride is 1 mg daily for all patients with type 2 diabetes and renal impairment [see Dosage and Administration (2.1)and Warnings and Precautions (5.1)].
A multiple-dose titration study was conducted in 16 patients with type 2 diabetes and renal impairment using doses ranging from 1 mg to 8 mg daily for 3 months. Baseline creatinine clearance ranged from 10 to 60 mL/min. The pharmacokinetics of glimepiride was evaluated in the multiple-dose titration study and the results were consistent with those observed in patients enrolled in a single-dose study. In both studies, the relative total clearance of glimepiride increased when kidney function was impaired. Both studies also demonstrated that the elimination of the two major metabolites was reduced in patients with renal impairment [see Clinical Pharmacology (12.3)].

10 OVERDOSAGE

An overdosage of glimepiride, as with other sulfonylureas, can produce severe hypoglycemia. Mild episodes of hypoglycemia can be treated with oral glucose. Severe hypoglycemic reactions constitute medical emergencies requiring immediate treatment. Severe hypoglycemia with coma, seizure, or neurological impairment can be treated with glucagon or intravenous glucose. Continued observation and additional carbohydrate intake may be necessary because hypoglycemia may recur after apparent clinical recovery [see Warnings and Precautions (5.1)] .

11 DESCRIPTION

Glimepiride tablets, USP are an oral sulfonylurea that contains the active ingredient glimepiride. Chemically, glimepiride is identified as 1-[[p-[2-(3-ethyl-4-methyl-2-oxo-3-pyrroline-1-carboxamido)ethyl]phenyl]sulfonyl]-3-(trans-4-methylcyclohexyl)urea (C24H34N4O5S) with a molecular weight of 490.62. Glimepiride USP is a white or almost white powder and is practically insoluble in water.
The structural formula is:

Glimepiride tablets, USP contain the active ingredient glimepiride and the following inactive ingredients: lactose monohydrate, magnesium stearate, microcrystalline cellulose, povidone, and sodium starch glycolate. In addition, 1 mg contains ferric oxide red, 2 mg contains ferric oxide yellow and FD&C blue No. 2, and 4 mg contains FD&C blue No. 2.

12 CLINICAL PHARMACOLOGY

12.1 Mechanism of Action

Glimepiride primarily lowers blood glucose by stimulating the release of insulin from pancreatic beta cells. Sulfonylureas bind to the sulfonylurea receptor in the pancreatic beta-cell plasma membrane, leading to closure of the ATP-sensitive potassium channel, thereby stimulating the release of insulin.

12.2 Pharmacodynamics

In healthy subjects, the time to reach maximal effect (minimum blood glucose concentrations) was approximately 2 to 3 hours after single oral doses of glimepiride. The effects of glimepiride on HbA1c, fasting plasma glucose, and postprandial glucose have been assessed in clinical trials [see Clinical Studies (14)] .

12.3 Pharmacokinetics

Absorption
Studies with single oral doses of glimepiride in healthy subjects and with multiple oral doses in patients with type 2 diabetes showed peak drug concentrations (Cmax) 2 to 3 hours postdose. When glimepiride was given with meals, the mean Cmaxand AUC (area under the curve) were decreased by 8% and 9%, respectively.
Glimepiride does not accumulate in serum following multiple dosing. The pharmacokinetics of glimepiride does not differ between healthy subjects and patients with type 2 diabetes. Clearance of glimepiride after oral administration does not change over the 1 mg to 8 mg dose range, indicating linear pharmacokinetics.
In healthy subjects, the intraindividual and interindividual variabilities of glimepiride pharmacokinetic parameters were 15% to 23% and 24% to 29%, respectively.
Distribution
After intravenous dosing in healthy subjects, the volume of distribution (Vd) was 8.8 L (113 mL/kg), and the total body clearance (CL) was 47.8 mL/min. Protein binding was greater than 99.5%.
Metabolism
Glimepiride is completely metabolized by oxidative biotransformation after either an intravenous or oral dose. The major metabolites are the cyclohexyl hydroxy methyl derivative (M1) and the carboxyl derivative (M2). Cytochrome P450 2C9 is involved in the biotransformation of glimepiride to M1. M1 is further metabolized to M2 by one or several cytosolic enzymes. M2 is inactive. In animals, M1 possesses about one-third of the pharmacological activity of glimepiride, but it is unclear whether M1 results in clinically meaningful effects on blood glucose in humans.
Excretion
When^14C-glimepiride was given orally to 3 healthy male subjects, approximately 60% of the total radioactivity was recovered in the urine in 7 days. M1 and M2 accounted for 80% to 90% of the radioactivity recovered in the urine. The ratio of M1 to M2 in the urine was approximately 3:2 in two subjects and 4:1 in one subject. Approximately 40% of the total radioactivity was recovered in feces. M1 and M2 accounted for about 70% (ratio of M1 to M2 was 1:3) of the radioactivity recovered in feces. No parent drug was recovered from urine or feces. After intravenous dosing in patients, no significant biliary excretion of glimepiride or its M1 metabolite was observed.
Specific Populations
Geriatric patients
A comparison of glimepiride pharmacokinetics in patients with type 2 diabetes ≤65 years and those >65 years was evaluated in a multiple-dose study using glimepiride 6 mg daily. There were no significant differences in glimepiride pharmacokinetics between the two age groups. The mean AUC at steady state for the older patients was approximately 13% lower than that for the younger patients; the mean weight-adjusted clearance for the older patients was approximately 11% higher than that for the younger patients.
Gender
There were no differences between males and females in the pharmacokinetics of glimepiride when adjustment was made for differences in body weight.
Race
No studies have been conducted to assess the effects of race on glimepiride pharmacokinetics but in placebo-controlled trials of glimepiride in patients with type 2 diabetes, the reduction in HbA1C was comparable in Caucasians (n=536), blacks (n=63), and Hispanics (n=63).
Renal impairment
In a single-dose, open-label study, glimepiride 3 mg was administered to patients with mild, moderate and severe renal impairment as estimated by creatinine clearance (CLcr): Group I consisted of 5 patients with mild renal impairment (CLcr >50 mL/min), Group II consisted of 3 patients with moderate renal impairment (CLcr=20 to 50 mL/min) and Group III consisted of 7 patients with severe renal impairment (CLcr <20 mL/min). Although glimepiride serum concentrations decreased with decreasing renal function, Group III had a 2.3-fold higher mean AUC for M1 and an 8.6-fold higher mean AUC for M2 compared to corresponding mean AUCs in Group I. The apparent terminal half-life (T1/2) for glimepiride did not change, while the half-lives for M1 and M2 increased as renal function decreased. Mean urinary excretion of M1 plus M2 as a percentage of dose decreased from 44.4% for Group I to 21.9% for Group II and 9.3% for Group III.
Hepatic impairment
It is unknown whether there is an effect of hepatic impairment on glimepiride pharmacokinetics because the pharmacokinetics of glimepiride has not been adequately evaluated in patients with hepatic impairment.
Obese patients
The pharmacokinetics of glimepiride and its metabolites were measured in a single-dose study involving 28 patients with type 2 diabetes who either had normal body weight or were morbidly obese. While the tmax, clearance and volume of distribution of glimepiride in the morbidly obese patients were similar to those in the normal weight group, the morbidly obese had lower Cmaxand AUC than those of normal body weight. The mean Cmax, AUC0-24, AUC0-∞values of glimepiride in normal vs. morbidly obese patients were 547±218 ng/mL vs. 410±124 ng/mL, 3210±1030 hours·ng/mL vs. 2820±1110 hours·ng/mL and 4000±1320 hours·ng/mL vs. 3280±1360 hours·ng/mL, respectively.
Drug Interactions
Aspirin
In a randomized, double-blind, two-period, crossover study, healthy subjects were given either placebo or aspirin 1 gram three times daily for a total treatment period of 5 days. On Day 4 of each study period, a single 1 mg dose of glimepiride was administered. The glimepiride doses were separated by a 14-day washout period. Coadministration of aspirin and glimepiride resulted in a 34% decrease in the mean glimepiride AUC and a 4% decrease in the mean glimepiride Cmax.
Colesevelam
Concomitant administration of colesevelam and glimepiride resulted in reductions in glimepiride AUC0-∞and Cmaxof 18% and 8%, respectively. When glimepiride was administered 4 hours prior to colesevelam, there was no significant change in glimepiride AUC0-∞or Cmax, -6% and 3%, respectively [ see Dosage and Administration (2.1) and Drug Interactions (7.4)].
Cimetidine and ranitidine
In a randomized, open-label, 3-way crossover study, healthy subjects received either a single 4 mg dose of glimepiride alone, glimepiride with ranitidine (150 mg twice daily for 4 days; glimepiride was administered on Day 3), or glimepiride with cimetidine (800 mg daily for 4 days; glimepiride was administered on Day 3). Coadministration of cimetidine or ranitidine with a single 4 mg oral dose of glimepiride did not significantly alter the absorption and disposition of glimepiride.
Propranolol
In a randomized, double-blind, two-period, crossover study, healthy subjects were given either placebo or propranolol 40 mg three times daily for a total treatment period of 5 days. On Day 4 of each study period, a single 2 mg dose of glimepiride was administered. The glimepiride doses were separated by a 14-day washout period. Concomitant administration of propranolol and glimepiride significantly increased glimepiride Cmax, AUC, and T1/2by 23%, 22%, and 15%, respectively, and decreased glimepiride CL/f by 18%. The recovery of M1 and M2 from urine was not changed.
Warfarin
In an open-label, two-way, crossover study, healthy subjects received 4 mg of glimepiride daily for 10 days. Single 25 mg doses of warfarin were administered 6 days before starting glimepiride and on Day 4 of glimepiride administration. The concomitant administration of glimepiride did not alter the pharmacokinetics of R-and S-warfarin enantiomers. No changes were observed in warfarin plasma protein binding. Glimepiride resulted in a statistically significant decrease in the pharmacodynamic response to warfarin. The reductions in mean area under the prothrombin time (PT) curve and maximum PT values during glimepiride treatment were 3.3% and 9.9%, respectively, and are unlikely to be clinically relevant.

13 NONCLINICAL TOXICOLOGY

13.1 Carcinogenesis, Mutagenesis, Impairment of Fertility

Studies in rats at doses of up to 5000 parts per million (ppm) in complete feed (approximately 340 times the maximum recommended human dose, based on surface area) for 30 months showed no evidence of carcinogenesis. In mice, administration of glimepiride for 24 months resulted in an increase in benign pancreatic adenoma formation that was dose-related and was thought to be the result of chronic pancreatic stimulation. No adenoma formation in mice was observed at a dose of 320 ppm in complete feed, or 46 to 54 mg/kg body weight/day. This is at least 28 times the maximum human recommended dose of 8 mg once daily based on surface area.
Glimepiride was non-mutagenic in a battery of in vitroand in vivomutagenicity studies (Ames test, somatic cell mutation, chromosomal aberration, unscheduled DNA synthesis, and mouse micronucleus test).
There was no effect of glimepiride on male mouse fertility in animals exposed up to 2500 mg/kg body weight (>1,500 times the maximum recommended human dose based on surface area). Glimepiride had no effect on the fertility of male and female rats administered up to 4000 mg/kg body weight (approximately 4,000 times the maximum recommended human dose based on surface area).

14 CLINICAL STUDIES

14.1 Monotherapy

A total of 304 patients with type 2 diabetes already treated with sulfonylurea therapy participated in a 14-week, multicenter, randomized, double-blind, placebo-controlled trial evaluating the safety and efficacy of glimepiride monotherapy. Patients discontinued their sulfonylurea therapy then entered a 3-week placebo washout period followed by randomization into 1 of 4 treatment groups: placebo (n=74), glimepiride 1 mg (n=78), glimepiride 4 mg (n=76), and glimepiride 8 mg (n=76). All patients randomized to glimepiride started 1 mg daily. Patients randomized to glimepiride 4 mg or 8 mg had blinded, forced titration of the glimepiride dose at weekly intervals, first to 4 mg and then to 8 mg, as long as the dose was tolerated, until the randomized dose was reached. Patients randomized to the 4 mg dose reached the assigned dose at Week 2. Patients randomized to the 8 mg dose reached the assigned dose at Week 3. Once the randomized dose level was reached, patients were to be maintained at that dose until Week 14. Approximately 66% of the placebo-treated patients completed the trial compared to 81% of patients treated with glimepiride 1 mg and 92% of patients treated with glimepiride 4 mg or 8 mg. Compared to placebo, treatment with glimepiride 1 mg, 4 mg, and 8 mg daily provided statistically significant improvements in HbA1C compared to placebo (Table 3).

Table 3: 14-Week Monotherapy Trial Comparing Glimepiride to Placebo in Patients Previously Treated With Sulfonylurea Therapya
 | Placebo (N=74) | Glimepiride
 | Placebo (N=74) | 1 mg (N=78) | 4 mg (N=76) | 8 mg (N=76)
HbA1C (%)
 | n=59 | n=65 | n=65 | n=68
Baseline (mean) | 8 | 7.9 | 7.9 | 8
Change from Baseline (adjusted meanb) | 1.5 | 0.3 | -0.3 | -0.4
Difference from Placebo (adjusted meanb) 95% confidence interval |  | -1.2* (-1.5, -0.8) | -1.8* (-2.1, -1.4) | -1.8* (-2.2, -1.5)
Mean Baseline Weight (kg)
 | n=67 | n=76 | n=75 | n=73
Baseline (mean) | 85.7 | 84.3 | 86.1 | 85.5
Change from Baseline (adjusted meanb) | -2.3 | -0.2 | 0.5 | 1
Difference from Placebo (adjusted meanb) 95% confidence interval |  | 2* (1.4, 2.7) | 2.8* (2.1, 3.5) | 3.2* (2.5, 4)
aIntent-to-treat population using last observation on study
bLeast squares mean adjusted for baseline value
*p <0.001

A total of 249 patients who were treatment-naive or who had received limited treatment with antidiabetic therapy in the past were randomized to receive 22 weeks of treatment with either glimepiride (n=123) or placebo (n=126) in a multicenter, randomized, double-blind, placebo-controlled, dose-titration trial. The starting dose of glimepiride was 1 mg daily and was titrated upward or downward at 2-week intervals to a goal FPG of 90 to 150 mg/dL. Blood glucose levels for both FPG and PPG were analyzed in the laboratory. Following 10 weeks of dose adjustment, patients were maintained at their optimal dose (1, 2, 3, 4, 6, or 8 mg) for the remaining 12 weeks of the trial. Treatment with glimepiride provided statistically significant improvements in HbA1C and FPG compared to placebo (Table 4).

Table 4: 22-Week Monotherapy Trial Comparing Glimepiride to Placebo in Patients Who Were Treatment-Naive or Who Had No Recent Treatment with Antidiabetic Therapya
 | Placebo (N=126) | Glimepiride (N=123)
HbA1C (%) | n=97 | n=106
Baseline (mean) | 9.1 | 9.3
Change from Baseline (adjusted meanb) | -1.1* | -2.2*
Difference from Placebo (adjusted meanb) 95% confidence interval | -1.1* (-1.5, -0.8)
Body Weight (kg)
 | n=122 | n=119
Baseline (mean) | 86.5 | 87.1
Change from Baseline (adjusted meanb) | -0.9 | 1.8
Difference from Placebo (adjusted meanb) 95% confidence interval | 2.7 (1.9, 3.6)
aIntent-to-treat population using last observation on study
bLeast squares mean adjusted for baseline value
*p <0.0001

16 HOW SUPPLIED/STORAGE AND HANDLING

Glimepiride tablets, USP are available in the following strengths and package sizes:
Glimepiride Tablets USP, 2 mg are light green to green colored, flat-faced, oblong uncoated tablets with notched sides at double bisect, debossed with “Y” and “32” on either side of the bisect on one face and plain on the other face.
Bottles of 30 NDC 72789-370-30

Store at20° to 25°C (68° to 77°F) [see USP Controlled Room Temperature].
Dispense in well-closed containers with safety closures.

17 PATIENT COUNSELING INFORMATION

Hypoglycemia

Explain the symptoms and treatment of hypoglycemia as well as conditions that predispose to hypoglycemia. Inform patients that their ability to concentrate and react may be impaired as a result of hypoglycemia and that this may present a risk in situations where these abilities are especially important, such as driving or operating other machinery [see Warnings and Precautions (5.1)] .

Hypersensitivity Reactions

Inform patients that hypersensitivity reactions may occur with glimepiride and that if a reaction occurs to seek medical treatment and discontinue glimepiride [see Warnings and Precautions (5.2)] .

Pregnancy

Advise females of reproductive potential to inform their prescriber of a known or suspected pregnancy [see Use in Specific Populations (8.1)] .

Lactation

Advise breastfeeding women taking glimepiride to monitor breastfed infants for signs of hypoglycemia (e.g., jitters, cyanosis, apnea, hypothermia, excessive sleepiness, poor feeding, seizures) [see Use in Specific Populations (8.2)].

Distributed by:
Rising Pharma Holdings, Inc.
East Brunswick, NJ 08816

Made in India
Code: TS/DRUGS/22/2009
Issued: 03/2021

PACKAGE LABEL-PRINCIPAL DISPLAY PANEL - 2 mg

Glimepiride
Tablets, USP
2 mg
ONCE A DAY
Rx only